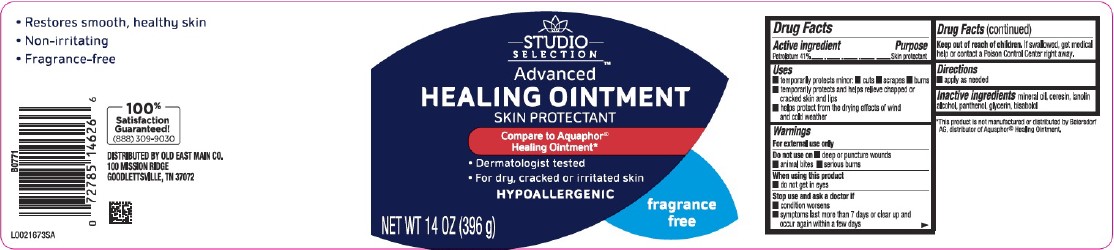 DRUG LABEL: Advanced Healing
NDC: 55910-965 | Form: OINTMENT
Manufacturer: Old East Main Co.
Category: otc | Type: HUMAN OTC DRUG LABEL
Date: 20260302

ACTIVE INGREDIENTS: PETROLATUM 410 mg/1 g
INACTIVE INGREDIENTS: MINERAL OIL; CERESIN; LANOLIN ALCOHOLS; PANTHENOL; GLYCERIN; LEVOMENOL

Studio Selection 247.000/247AA-AC
Healing Ointment for Dry and Cracked Skin

Active Ingredient

Petrolatum 41%

Purpose

Skin protectant

Uses

- temporarily protects minor:
- cuts
- scrapes
- burns
- temporarily protects and helps relieve chapped or cracked skin and lips
- helps protect from the drying effects of wind and cold weather

Warnings

For external use only

Do not use on

- deep or puncture wounds
- animal bites
- serious burns

When using this product

- do not get into eyes

Stop use and ask a doctor

- condition worsens
- symptoms last more than 7 days or clear up and occur again within a few days

Keep out of reach of children.

If swallowed, get medical help or contact a Poison Control Center right away.

Directions

- apply as needed

Inactive ingredients

mineral oil, cersin, lanolin alcohol, panthenol, glycerin, bisabolol

Disclaimer

*This product is not manufactured or distributed by Beiersdorf AG, distributor of Aquapor® Healing Ointment.

Claims

- Restores smooth, healthy skin
- Non-irritating
- Fragrance-free

ADVERSE REACTIONS SECTION

100% SATISFACTION GUARANTEED!

(888)309-9030

DISTRIBUTED BY Old East Main Co.

100 MISSION RIDGE

GOODLETTSVILLE, TN 37072

Principal Display Panel

STUDIO SELECTION™

Advanced

HEALING OINTMENT

SKIN PROTECTANT

Compare to Aquapor®Healing Ointment*

- Dermatologist tested
- For dry, cracked or irritated skin

HYPOALLERGENIC
fragrance free

HYPOALLERGENIC

NET WT 14 OZ (396 g)